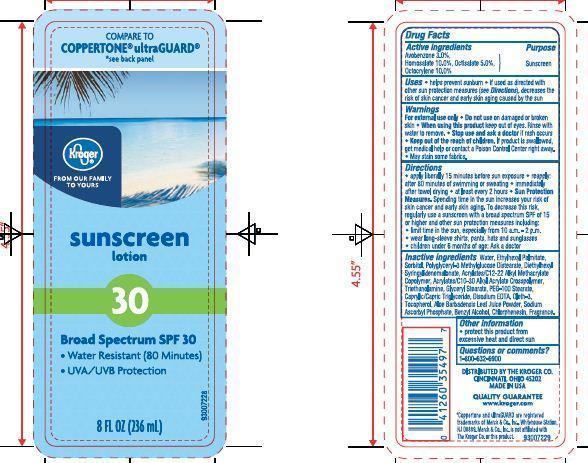 DRUG LABEL: Kroger Sport Sunscreen
NDC: 30142-938 | Form: LOTION
Manufacturer: THE KROGER CO
Category: otc | Type: HUMAN OTC DRUG LABEL
Date: 20140627

ACTIVE INGREDIENTS: AVOBENZONE 2 g/100 g; HOMOSALATE 10 g/100 g; OCTISALATE 5 g/100 g; OCTOCRYLENE 4 g/100 g; OXYBENZONE 5 g/100 g
INACTIVE INGREDIENTS: ETHYLHEXYL PALMITATE; SORBITOL; DIETHYLHEXYL SYRINGYLIDENEMALONATE; TROLAMINE; GLYCERYL MONOSTEARATE; PEG-100 STEARATE; TRICAPRIN; EDETATE DISODIUM; OLETH-3; TOCOPHEROL; ALOE VERA LEAF; SODIUM ASCORBYL PHOSPHATE; BENZYL ALCOHOL; CHLORPHENESIN

Drug Facts

Active ingredients

Avobenzone 2.0 %

Homosalate 10.0%

Octisalate 5.0%

Octocrylene 4.0%

Oxybenzone 5.0%

Purpose

Sunscreen

Uses

- Helps prevent sunburn
- If used as directed with other sun protection measures (see Directions), decrease the risk of skin cancer and early skin aging caused by the sun.

Warnings

For external use only

When using this product

- keep out of eyes. Rinse with water to remove.

Stop use and ask a doctor if

- rash or irritation develops and lasts

Keep out of reach of children.

If swallowed get medical help or contact a Poison Control Center right away.

Other information

- protect this product from excessive heat and direct sun

Directions

- apply liberally 15 minutes before sun exposure
- reapply
- after 80 minutes of swimming or sweating
- immediately after towel drying
- at least every 2 hours
- Sun Protection Measures: Spending time in the sun increases your risk of skin cancer and early skin aging. To decrease this risk, regularly use a sunscreen with a broad spectrum SPF of 15 or higher and other sun protection measures including:
- limit time in the sun, especially from 10 a.m. - 2 p.m.
- wear long-sleeve shirts, pants, hats and sunglasses
- children under 6 months of age: Ask a doctor

Inactive ingredients

Water, Ethylhexyl Palmitate, Sorbitol, Polyglyceryl-3 Methylglucose Distearate, Diethylhexyl Syringylidenemalonate, Acrylates/C12-22 Alkyl Methacrylate Copolymer, Acrylates/C10-30 Alkyl Acrylate Crosspolymer, Triethanolamine, Glyceryl Stearate, PEG-100 Stearate, Caprylic/Capric Triglyceride, Disodium EDTA, Oleth-3, Tocopherol, Aloe Barbadensis Leaf Juice Powder, Sodium Ascorbyl Phosphate, Benzyl Alcohol, Chlorphenesin, Fragrance.

Principal Display Panel

COMPARE TO COPPERTONE SPORT

see back panel

kroger

FROM OUR FAMILY TO YOURS

sunscreen lotion

30

Broad Spectrum SPF 30

- Water Resistant (80 Minutes)
- Wont Run into Eyes

8 FL OZ (236ml)